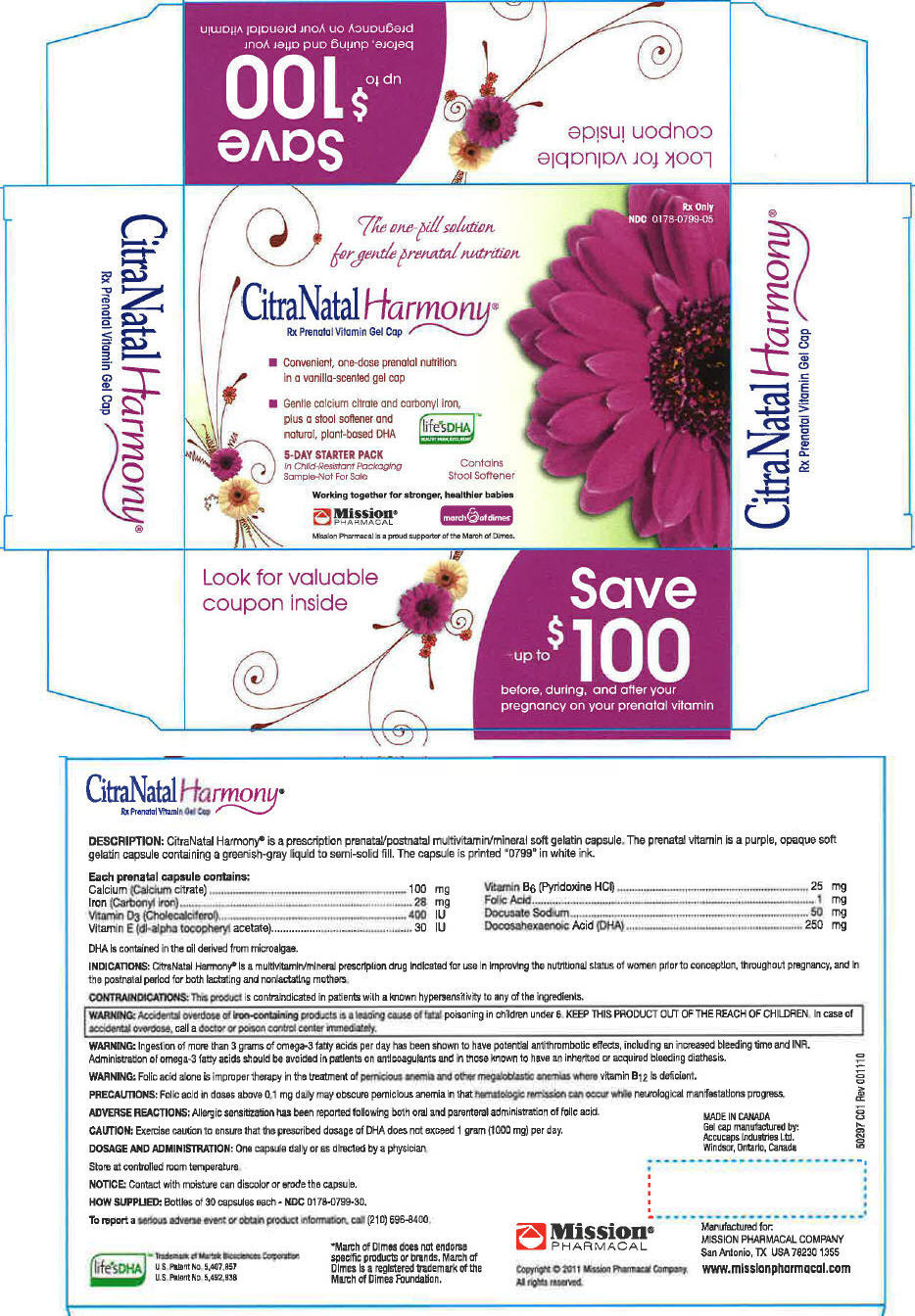 DRUG LABEL: CitraNatal Harmony
NDC: 0178-0799 | Form: CAPSULE, GELATIN COATED
Manufacturer: MISSION PHARMACAL COMPANY
Category: prescription | Type: HUMAN PRESCRIPTION DRUG LABEL
Date: 20110603

ACTIVE INGREDIENTS: Calcium citrate 100 mg/1 1; Iron pentacarbonyl 28 mg/1 1; Cholecalciferol 400 [iU]/1 1; .Alpha.-tocopherol, DL- 30 [iU]/1 1; Pyridoxine hydrochloride 25 mg/1 1; Folic Acid 1 mg/1 1; Docusate Sodium 50 mg/1 1; Doconexent 250 mg/1 1

CitraNatal Harmony®
Rx Prenatal Vitamin Gel Cap

DESCRIPTION

CitraNatal Harmony® is a prescription prenatal/postnatal multivitamin/mineral soft gelatin capsule. The prenatal vitamin is a purple, opaque soft gelatin capsule containing a greenish-gray liquid to semi-solid fill. The capsule is printed "0799" in white ink.

Each prenatal capsule contains:

Calcium (Calcium citrate) | 100 mg |  | Vitamin B6 (Pyridoxine HCl) | 25 mg
Iron (Carbonyl iron) | 28 mg |  | Folic Acid | 1 mg
Vitamin D3 (Cholecalciferol) | 400 IU |  | Docusate Sodium | 50 mg
Vitamin E (dl-alpha tocopheryl acetate) | 30 IU |  | Docosahexaenoic Acid (DHA) | 250 mg

DHA is contained in the oil derived from microalgae.

INDICATIONS

CitraNatal Harmony® is a multivitamin/mineral prescription drug indicated for use in improving the nutritional status of women prior to conception, throughout pregnancy, and in the postnatal period for both lactating and nonlactating mothers.

CONTRAINDICATIONS

This product is contraindicated in patients with a known hypersensitivity to any of the ingredients.

WARNING

Accidental overdose of iron-containing products is a leading cause of fatal poisoning in children under 6. KEEP THIS PRODUCT OUT OF THE REACH OF CHILDREN. In case of accidental overdose, call a doctor or poison control center immediately.

WARNING

Ingestion of more than 3 grams of omega-3 fatty acids per day has been shown to have potential antithrombotic effects, including an increased bleeding time and INR. Administration of omega-3 fatty acids should be avoided in patients on anticoagulants and in those known to have an inherited or acquired bleeding diathesis.

WARNING

Folic acid alone is improper therapy in the treatment of pernicious anemia and other megaloblastic anemias where vitamin B12 is deficient.

PRECAUTIONS

Folic acid in doses above 0.1 mg daily may obscure pernicious anemia in that hematologic remission can occur while neurological manifestations progress.

ADVERSE REACTIONS

Allergic sensitization has been reported following both oral and parenteral administration of folic acid.

CAUTION: Exercise caution to ensure that the prescribed dosage of DHA does not exceed 1 gram (1000 mg) per day.

DOSAGE AND ADMINISTRATION

One capsule daily or as directed by a physician.

Store at controlled room temperature.

NOTICE: Contact with moisture can discolor or erode the capsule.

HOW SUPPLIED

Bottles of 30 capsules each - NDC 0178-0799-30.

To report a serious adverse event or obtain product information, call (210) 696-8400.

life'sDHA™

Trademark of Martek Biosciences Corporation
U.S. Patent No. 5,407,857
U.S. Patent No. 5,492,938

*March of Dimes does not endorse specific products or brands. March of Dimes is a registered trademark of the March of Dimes Foundation.

Manufactured for:
MISSION PHARMACAL COMPANY
San Antonio, TX USA 78230 1355

www.missionpharmacal.com

Copyright © 2011 Mission Pharmacal Company. All rights reserved.

PRINCIPAL DISPLAY PANEL - 30 Capsule Bottle Carton

The one-pill solution
for gentle prenatal nutrition

Rx Only
NDC 0178-0799-05

CitraNatal Harmony®
Rx Prenatal Vitamin Gel Cap

- Convenient, one-dose prenatal nutrition
  in a vanilla-scented gel cap
- Gentle calcium citrate and carbonyl iron,
  plus a stool softener and
  natural, plant-based DHA

life'sDHA ™
HEALTHY BRAIN, EYES, HEART

5-DAY STARTER PACK
In Child-Resistant Packaging
Sample–Not For Sale

Contains
Stool Softener

Working together for stronger, healthier babies

Mission®
PHARMACAL

march of dimes

Mission Pharmacal is a proud supporter of the March of Dimes.